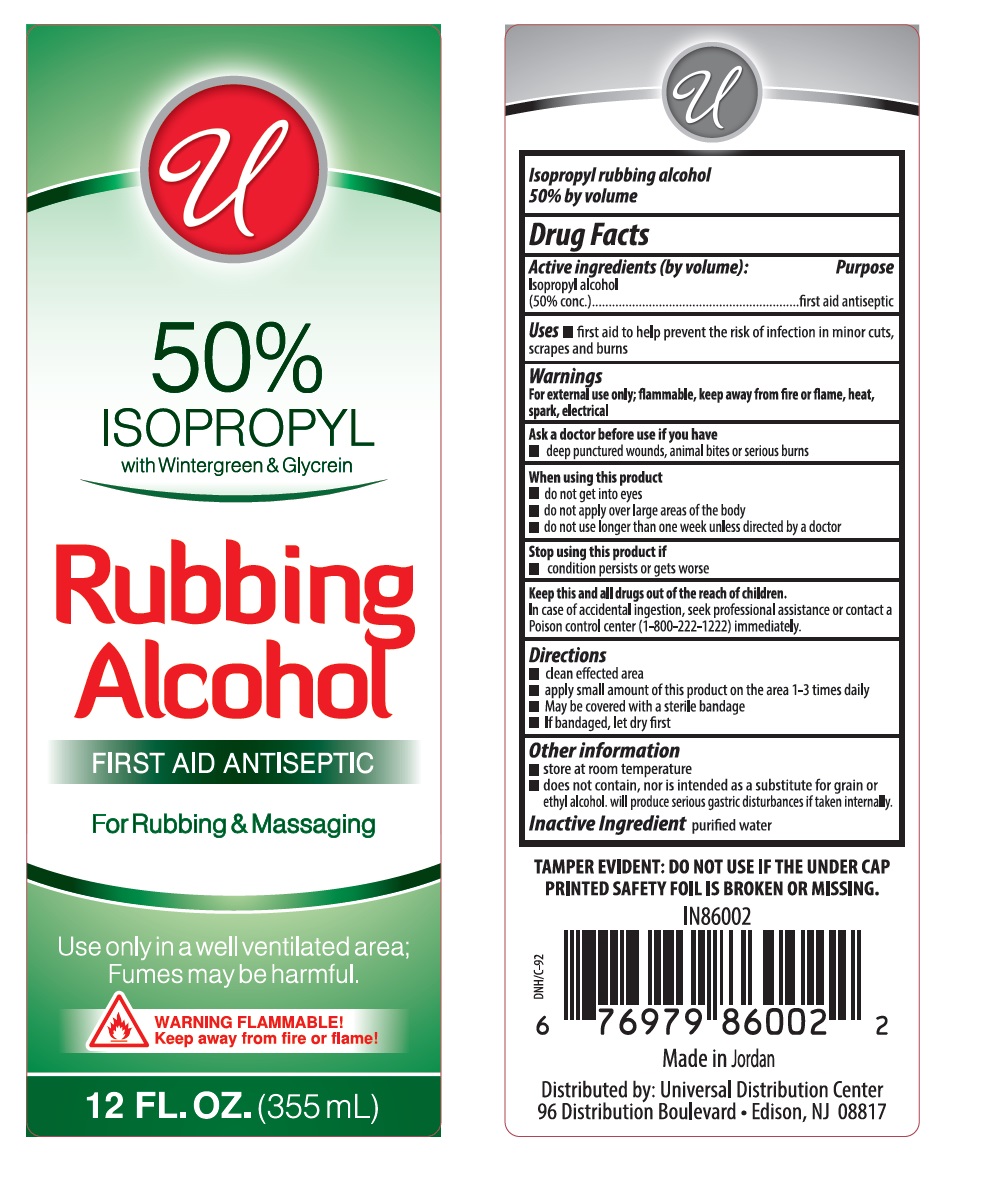 DRUG LABEL: Allure Isopropyl Rubbing Alcohol With Wintergreen
NDC: 52000-002 | Form: LIQUID
Manufacturer:  Universal Distribution Center LLC
Category: otc | Type: HUMAN OTC DRUG LABEL
Date: 20241212

ACTIVE INGREDIENTS: ISOPROPYL ALCOHOL 50 mL/100 mL
INACTIVE INGREDIENTS: WATER

ALLURE ISOPROPYL RUBBING ALCOHOL WITH WINTERGREEN

Active Ingredients

Isopropyl alcohol (50% conc.)

Purpose

Topical antimicrobial

Uses

- to decrease germs in minor cuts and scrapes.
- helps relieve minor muscular aches due to exertion.

Warnings

For external use only

- flammable, keep away from fire or flame, heat, spark, electrical.

Ask a doctor before use if you have

deep or puncture wounds, animal bites or serious burns.

When using this product

- do not get into eyes
- do not apply over large areas of body
- do not use longer than one week unless directed by a doctor

Stop using this product if

- condition persists or gets worse

Keep this and all drugs out of the reach of children

In case of accidental ingestion, seek professional assistance or contact a Poison control center (1-800-222-1212) immediately

Directions

- clean affected area
- apply a small amount of this product on the area 1-3 times daily
- may be covered with a sterile bandage
- if bandaged, let dry first

Other information

- store at room temperature
- does not contain, nor is intended as a substitute for grain or ethyl alcohol, will produce serious gastric disturbance if taken internally

Inactive ingredient

purified water